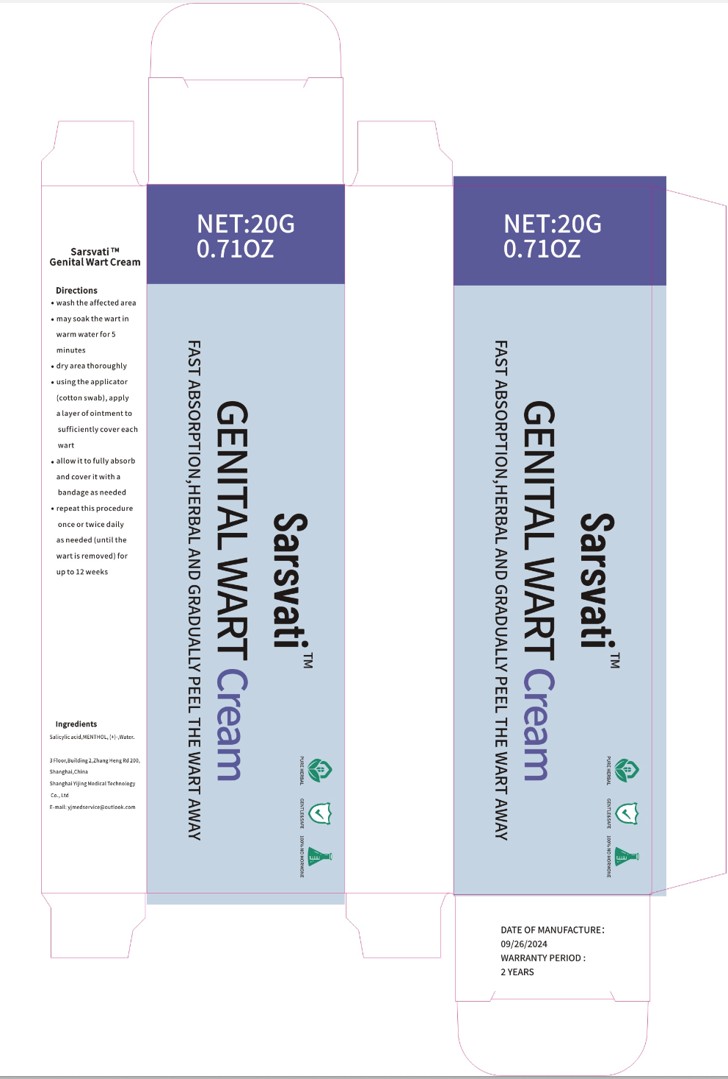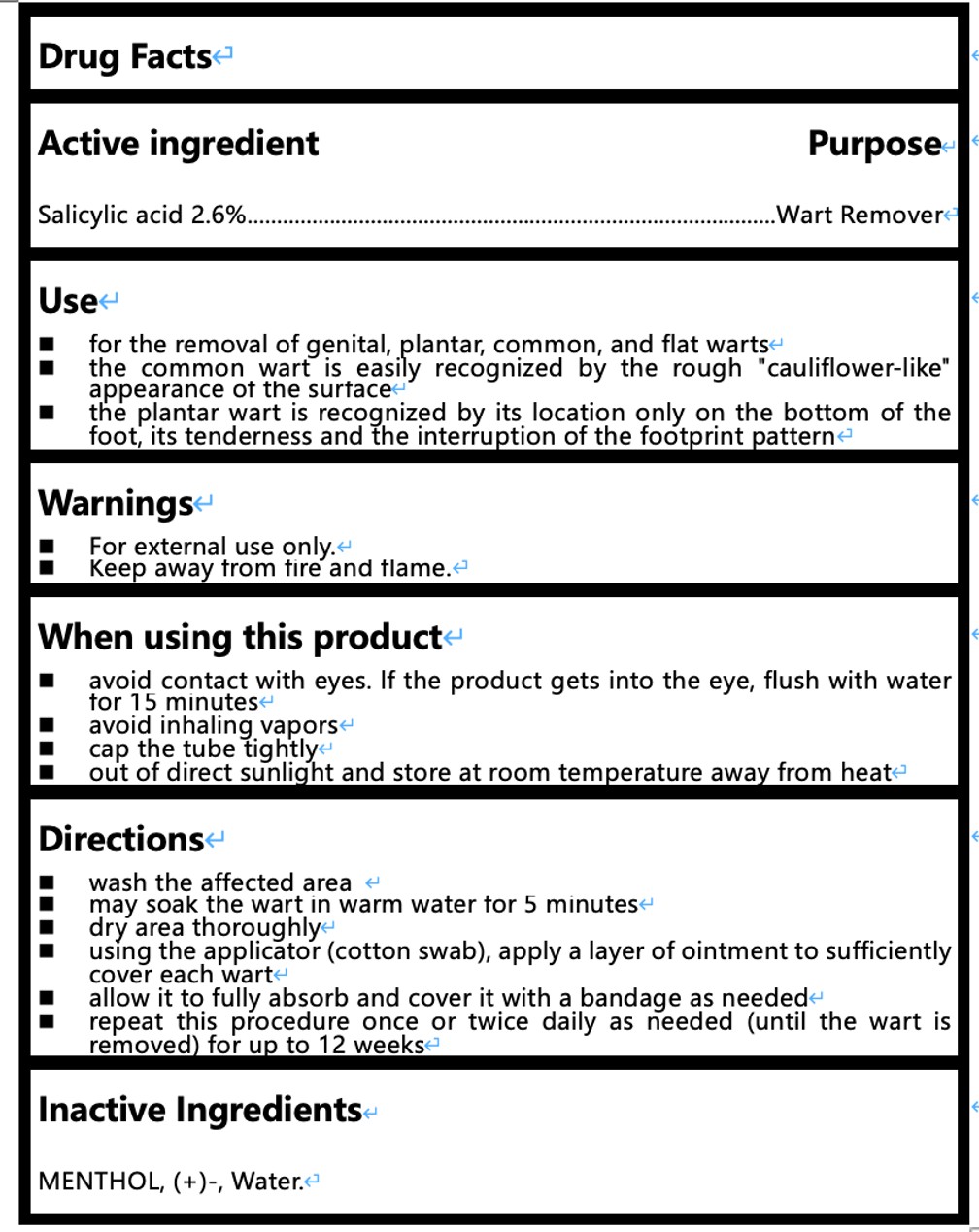 DRUG LABEL: Genital Wart Remover Cream
NDC: 85157-001 | Form: CREAM
Manufacturer: Shanghai Yijing Medical Technology Co., Ltd.
Category: otc | Type: HUMAN OTC DRUG LABEL
Date: 20250114

ACTIVE INGREDIENTS: SALICYLIC ACID 2.6 g/100 g
INACTIVE INGREDIENTS: WATER; MENTHOL, (+)-

Genital Wart Remover Cream

ACTIVE INGREDIENT

Salicylic Acid 2.6%

PURPOSE

Wart Remover

KEEP OUT OF REACH OF CHILDREN SECTION

INDICATIONS AND USAGE

for the removal of genital, plantar common, and flat wartse

the common wart is easily recognized by the rough "cauliflower-like

appearance ot the surtace←the plantar wart is recognized by its location only on the bottom of the

foot, its tenderness and the interruption of the footprint pattern

WARNINGS

For external use only.

Keep away trom tire and tlame.

WHEN USING

avoid contact with eyes. lf the product gets into the eye, flush with water for 15 minutes

avoid inhaling vapors

cap the tube tightlye

out of direct sunlight and store at room temperature away from heat

DOSAGE AND ADMINISTRATION

wash the affected area

may soak the wart in warm water for 5 minutes

dry area thoroughly

using the applicator (cotton swab), apply a layer of ointment to sufficientlycover each wart

allow it to fully absorb and cover it with a bandage as needed

repeat this procedure once or twice daily as needed (until the wart is removed)for up to 12 weeks

INACTIVE INGREDIENT

WATER, MENTHOL, (+)-